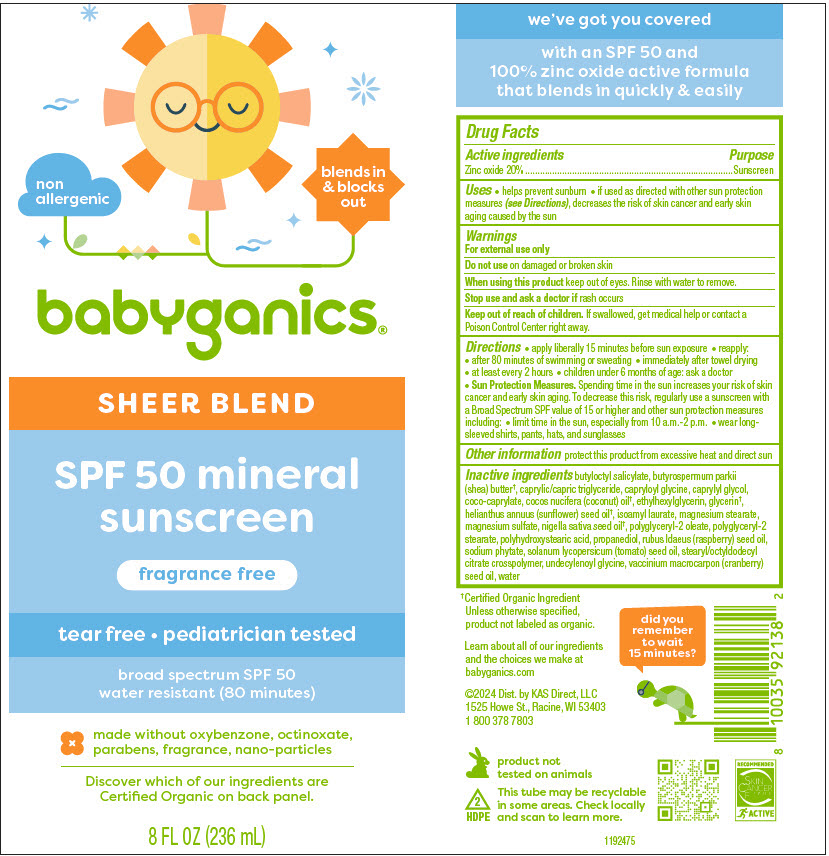 DRUG LABEL: Babyganics Sheer Blend SPF50 Mineral Sunscreen
NDC: 59062-2202 | Form: LOTION
Manufacturer: KAS Direct LLC dba BabyGanics
Category: otc | Type: HUMAN OTC DRUG LABEL
Date: 20241220

ACTIVE INGREDIENTS: Zinc Oxide 20 g/100 mL
INACTIVE INGREDIENTS: Water; Coco-Caprylate; MEDIUM-CHAIN TRIGLYCERIDES; COCONUT OIL; Isoamyl laurate; MAGNESIUM STEARATE; Shea Butter Ethyl Esters; MAGNESIUM SULFATE, UNSPECIFIED FORM; POLYHYDROXYSTEARIC ACID (2300 MW); Butyloctyl Salicylate; Polyglyceryl-2 oleate; Polyglyceryl-2 stearate; Propanediol; Stearyl/Octyldodecyl Citrate Crosspolymer; Undecylenoyl Glycine; Ethylhexylglycerin; Glycerin; PHYTATE SODIUM; SUNFLOWER SEED; TOMATO SEED OIL; CRANBERRY SEED; NIGELLA SATIVA SEED OIL; RUBUS IDAEUS SEED; Capryloyl Glycine; Caprylyl Glycol

Babyganics® Sheer Blend SPF50 Mineral Sunscreen

Drug Facts

Active ingredients

Zinc oxide 20%

Purpose

Sunscreen

Uses

- helps prevent sunburn
- if used as directed with other sun protection measures (see Directions), decreases the risk of skin cancer and early skin aging caused by the sun

Warnings

For external use only

Do not use on damaged or broken skin

When using this product keep out of eyes. Rinse with water to remove.

Stop use and ask a doctor if rash occurs

Keep out of reach of children. If swallowed, get medical help or contact a Poison Control Center right away.

Directions

- apply liberally 15 minutes before sun exposure
- reapply:
  - after 80 minutes of swimming or sweating
  - immediately after towel drying
  - at least every 2 hours
  - children under 6 months of age: ask a doctor
- Sun Protection Measures. Spending time in the sun increases your risk of skin cancer and early skin aging. To decrease this risk, regularly use a sunscreen with a Broad Spectrum SPF value of 15 or higher and other sun protection measures including:
  - limit time in the sun, especially from 10 a.m.-2 p.m.
  - wear long-sleeved shirts, pants, hats, and sunglasses

Other information

protect this product from excessive heat and direct sun

Inactive ingredients

butyloctyl salicylate, butyrospermum parkii (shea) butter [Certified Organic Ingredient Unless otherwise specified, product not labeled as organic.] , caprylic/capric triglyceride, capryloyl glycine, caprylyl glycol, coco-caprylate, cocos nucifera (coconut) oil, ethylhexylglycerin, glycerin, helianthus annuus (sunflower) seed oil, lsoamyl laurate, magnesium stearate, magnesium sulfate, nigella sativa seed oil, polyglyceryl-2 oleate, polyglyceryl-2 stearate, polyhydroxystearic acid, propanediol, rubus ldaeus (raspberry) seed oil, sodium phytate, solanum lycopersicum (tomato) seed oil, stearyl/octyldodecyl citrate crosspolymer, undecylenoyl glycine, vaccinium macrocarpon (cranberry) seed oil, water

Dist. by KAS Direct, LLC
1525 Howe St., Racine, WI 53403

PRINCIPAL DISPLAY PANEL - 236 mL Tube Label

non
allergenic

blends in
& blocks
out

babyganics®

SHEER BLEND

SPF 50 mineral
sunscreen

fragrance free

tear free • pediatrician tested

broad spectrum SPF 50
water resistant (80 minutes)

made without oxybenzone, octinoxate,
parabens, fragrance, nano-particles

Discover which of our ingredients are
Certified Organic on back panel.

8 FL OZ (236 mL)